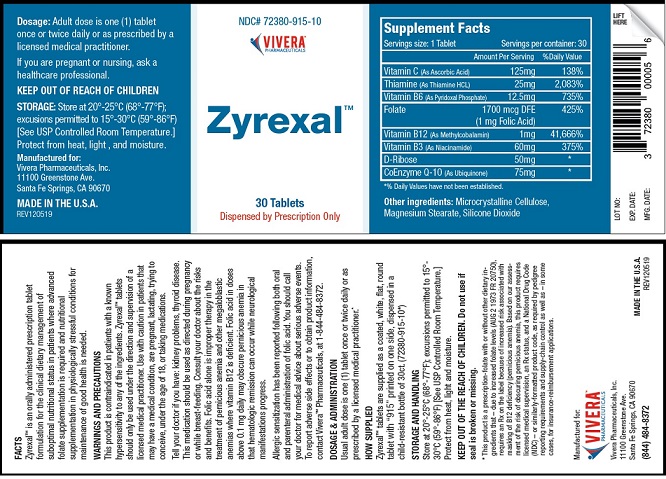 DRUG LABEL: Zyrexal
NDC: 72380-915 | Form: TABLET
Manufacturer: Vivera Pharmaceuticals, Inc.
Category: prescription | Type: HUMAN PRESCRIPTION DRUG LABEL
Date: 20200210

ACTIVE INGREDIENTS: ASCORBIC ACID 125 mg/1 1; THIAMINE HYDROCHLORIDE 25 mg/1 1; PYRIDOXINE 12.5 mg/1 1; FOLIC ACID 1 mg/1 1; METHYLCOBALAMIN 1 mg/1 1; NIACINAMIDE 60 mg/1 1; .BETA.-D-RIBOSE 50 mg/1 1; UBIDECARENONE 75 mg/1 1
INACTIVE INGREDIENTS: MICROCRYSTALLINE CELLULOSE; MAGNESIUM STEARATE; SILICON DIOXIDE

ZyrexalTM

FACTS

Zyrexal™ is an orally administered prescription tablet
formulation for the clinical dietary management of
suboptimal nutritional status in patients where advanced
folate supplementation is required and nutritional
supplementation in physiologically stressful conditions for
maintenance of good health is needed.

WARNINGS AND PRECAUTIONS

This product is contraindicated in patients with a known
hypersensitivity to any of the ingredients. Zyrexal™ tablets
should only be used under the direction and supervision of a
licensed medical practitioner. Use with caution in patients that
may have a medical condition, are pregnant, lactating, trying to
conceive, under the age of 18, or taking medications.

Tell your doctor if you have: kidney problems, thyroid disease.
This medication should be used as directed during pregnancy
or while breast-feeding. Consult your doctor about the risks
and benefits. Folic acid alone is improper therapy in the
treatment of pernicious anemia and other megaloblastic
anemias where vitamin B12 is deficient. Folic acid in doses
above 0.1 mg daily may obscure pernicious anemia in
that hematologic remission can occur while neurological
manifestations progress.

Allergic sensitization has been reported following both oral
and parenteral administration of folic acid. You should call
your doctor for medical advice about serious adverse events.
To report adverse side effects or to obtain product information,
contact Vivera™ Pharmaceuticals, at 1-844-484-8372.

DOSAGE & ADMINISTRATION

Usual adult dose is one (1) tablet once or twice daily or as
prescribed by a licensed medical practitioner.*

HOW SUPPLIED
Zyrexal™ tablets are supplied as a coated, white, flat, round
tablet with “915” printed on one side, dispensed in a
child-resistant bottle of 30ct. (72380-915-10*)

STORAGE AND HANDLING
Store at 20°-25°C (68°-77°F); excursions permitted to 15°-
30°C (59°-86°F) [See USP Controlled Room Temperature.]
Protect from heat, light and moisture.

PREGNANCY

If you are pregnant or nursing, ask a
healthcare professional.

OTHER SAFETY INFORMATION

KEEP OUT OF THE REACH OF CHILDREN. Do not use if
seal is broken or missing.

OTHER SAFETY INFORMATION

* This product is a prescription-folate with or without other dietary in-
gredients that – due to increased folate levels (AUG 2 1973 FR 20750),
requires an Rx on the label because of increased risk associated with
masking of B12 deficiency (pernicious anemia). Based on our assess-
ment of the risk of obscuring pernicious anemia, this product requires
licensed medical supervision, an Rx status, and a National Drug Code
(NDC) – or similarly-formatted product code, as required by pedigree
reporting requirements and supply-chain control as well as – in some
cases, for insurance-reimbursement applications.

Package Label

NDC# 72380-915-10

VIVERA™
PHARMACEUTICALS

Zyrexal™

30 Tablets

Dispensed by Prescription Only

Supplement Facts
Servings size: 1 Tablet Servings per container: 30
Amount Per Serving %Daily Value
Vitamin C (As Ascorbic Acid) 125mg 138%
Thiamine (As Thiamine HCL) 25mg 2,083%
Vitamin B6 (As Pyridoxal Phosphate) 12.5mg 735%
Folate 1700 mcg DFE 425%
(1 mg Folic Acid)
Vitamin B12 (As Methylcobalamin) 1mg 41,666%
Vitamin B3 (As Niacinamide) 60mg 375%
D-Ribose 50mg *
CoEnzyme Q-10 (As Ubiquinone) 75mg *

* % Daily Values have not been established.

Other ingredients: Microcrystalline Cellulose,
Magnesium Stearate, Silicone Dioxide

Dosage: Adult dose is one (1) tablet
once or twice daily or as prescribed by a
licensed medical practitioner.

If you are pregnant or nursing, ask a
healthcare professional.

KEEP OUT OF REACH OF CHILDREN

STORAGE: Store at 20°-25°C (68°-77°F);
excusions permitted to 15°-30°C (59°-86°F)
[See USP Controlled Room Temperature.]
Protect from heat, light , and moisture.

Manufactured for:
Vivera Pharmaceuticals, Inc.
11100 Greenstone Ave.
Santa Fe Springs, CA 90670

MADE IN THE U.S.A.

REV120519

LOT NO:
EXP. DATE:
MFG. DATE:

3 72380 00005 6

RES